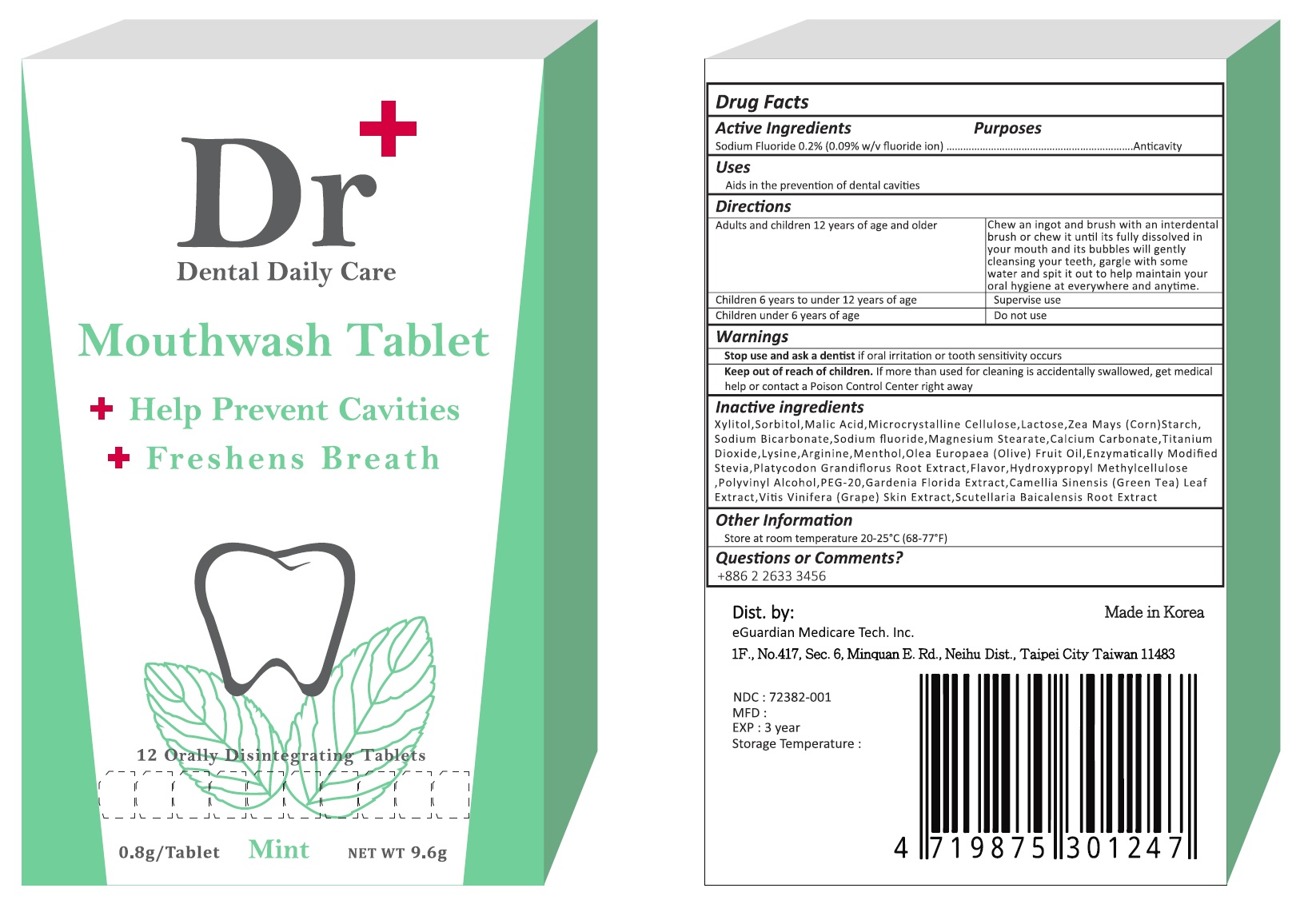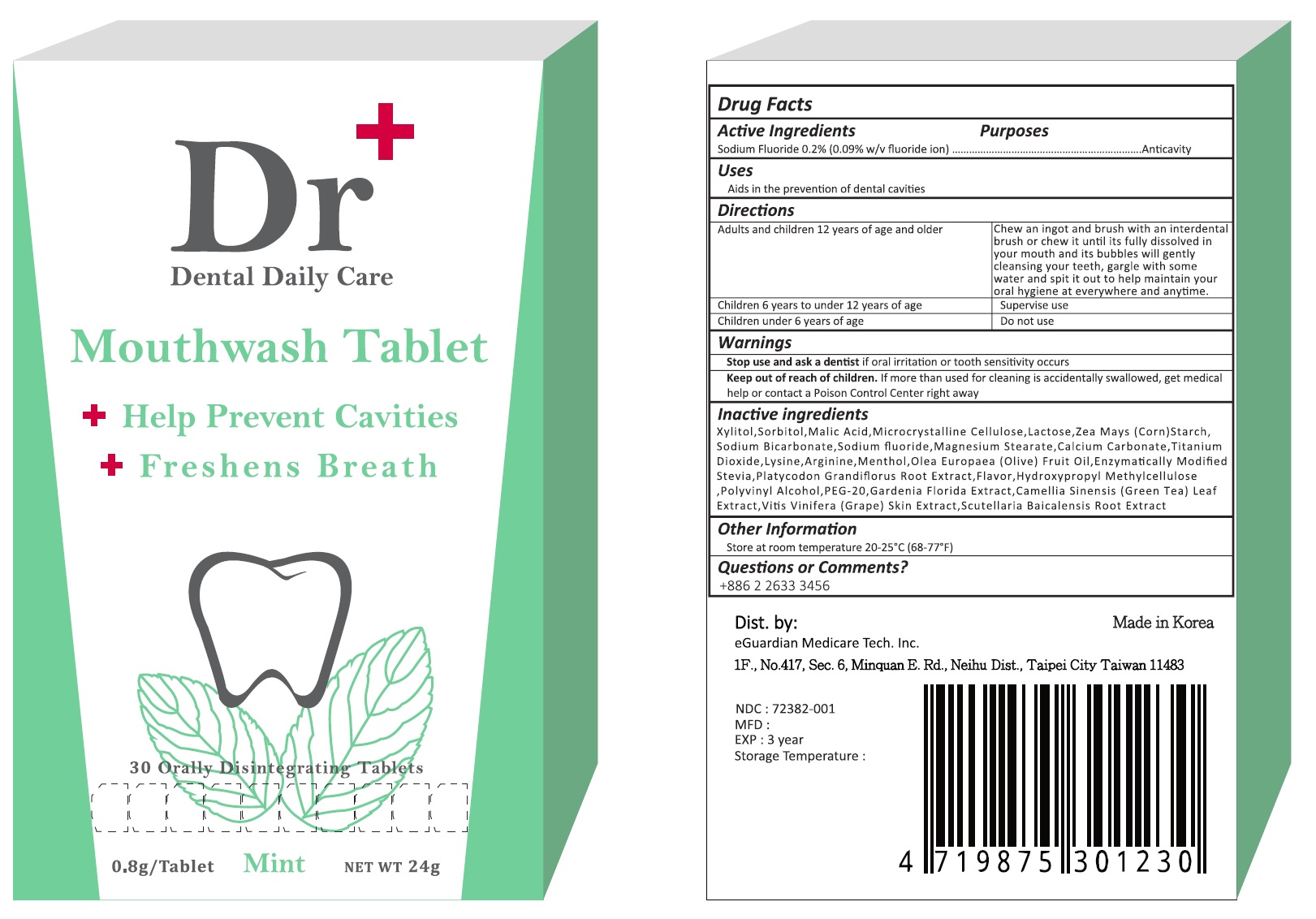 DRUG LABEL: Dr Plus Dental Daily Care
NDC: 72382-001 | Form: TABLET, ORALLY DISINTEGRATING
Manufacturer: EGUARDIAN MEDICARE TECH INC.
Category: otc | Type: HUMAN OTC DRUG LABEL
Date: 20180814

ACTIVE INGREDIENTS: SODIUM FLUORIDE 2 mg/1 g
INACTIVE INGREDIENTS: XYLITOL; SORBITOL; MALIC ACID; LACTOSE, UNSPECIFIED FORM; STARCH, CORN; SODIUM BICARBONATE; MAGNESIUM STEARATE; CALCIUM CARBONATE; TITANIUM DIOXIDE; LYSINE; ARGININE; MENTHOL, UNSPECIFIED FORM; OLIVE OIL; PLATYCODON GRANDIFLORUS ROOT; POLYVINYL ALCOHOL, UNSPECIFIED; POLYETHYLENE GLYCOL 1000; GARDENIA JASMINOIDES WHOLE; GREEN TEA LEAF; VITIS VINIFERA ANTHOCYANINS; SCUTELLARIA BAICALENSIS ROOT

Dr Plus Dental Daily Care

Drug Facts

Active ingredient

Sodium Fluoride 0.2% (0.09% w/v fluoride ion)

Purpose

Anticavity

Use

Aids in the prevention of dental cavities

Warnings

Stop use and ask a dentist if oral irritation or tooth sensitivity occurs.

Keep out of reach of children. If more than used for cleaning is accidentally swallowed, get medical help or contact a Poison Control Center right away.

DOSAGE AND ADMINISTRATION

adults and children 12 years and older - Chew an ingot and brush with an interdental brush or chew it until its fully dissolved in your mouth and its bubbles will gently cleansing your teeth, gargle with some water and spit it out to help maintain your oral hygiene at everywhere and anytime.

children 6 years to under 12 years of age - Supervise use.

children under 6 years - Do not use

Inactive ingredients

Xylitol, Sorbitol, Malic Acid, Microcrystalline Cellulose, Lactose, Zea Mays (Corn) Starch, Sodium Bicarbonate, Magnesium Steartae, Calcium Carbonate, Titanium Dioxide, Lysine, Arginine, Menthol, Olea Europaea (Olive) Fruit Oil, Enzymatically Modified Stevia, Platycodon Grandiflorus Root Extract, Flavor, Hydroxypropyle Methylcellulose, Polyvinyl Alcohol, PEG-20, Gardenia Floride Extract, Camellia Sinensis (Green Tea) Leaf Extract, Vitis Vinifera (Grape) Skin Extract, Scutellaria Baicalensis Root Extract

Questions or comments? +886 2 2633 3456